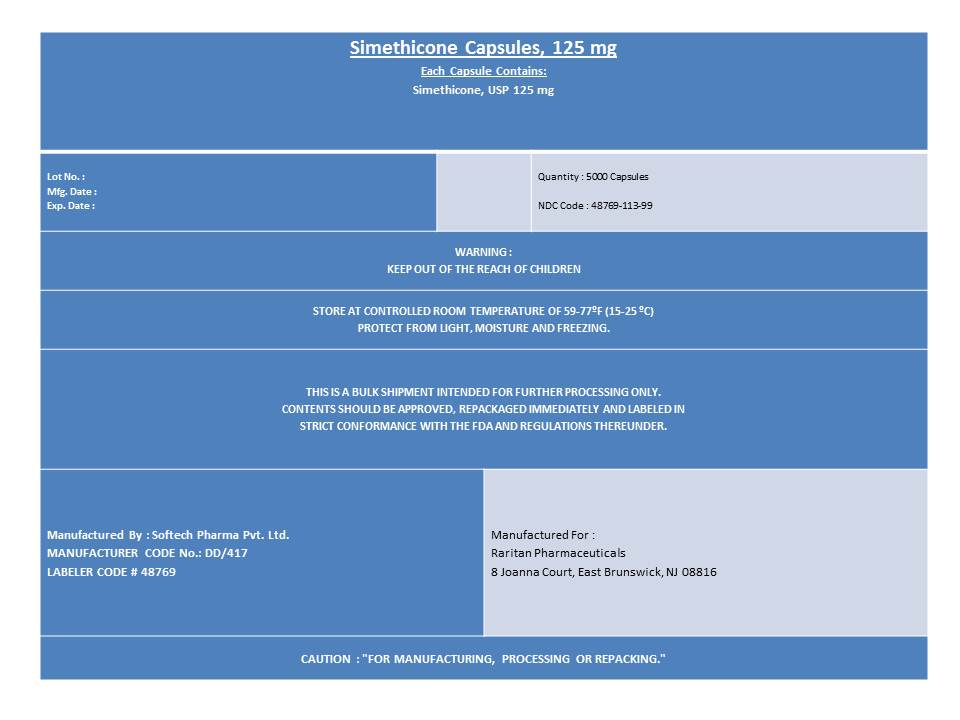 DRUG LABEL: Simethicone
NDC: 48769-113 | Form: CAPSULE, LIQUID FILLED
Manufacturer: Softech Pharma Pvt. Ltd
Category: otc | Type: HUMAN OTC DRUG LABEL
Date: 20120629

ACTIVE INGREDIENTS: Dimethicone 125 mg/1 1
INACTIVE INGREDIENTS: D&C YELLOW NO. 10; FD&C BLUE NO. 1; FD&C RED NO. 40; GELATIN; GLYCERIN; MANNITOL; PEPPERMINT OIL; WATER ; SORBITAN; SORBITOL; TITANIUM DIOXIDE

Simethicone Capsules, 125 mg

Active ingredient (per soft gel)

Simethicone 125 mg

Purpose

Antigas

Uses

Relieves pressure and bloating commonly referred to as gas

Warnings

Keep out of reach of children

Directions

- Do not exceed 4 softgels in 24 hours
- Adults: swallow with water 1 or 2 softgels as needed after meals and at bedtime

Other information

store at 20^0 - 25^0C

Inactive ingredients

D and C yellow 10, FD and C blue 1, FD and C red 40, gelatin, glycerin, mannitol, peppermint oil, purified water, sorbitan, sorbitol, titanium dioxide

Keep out of Reach of Children